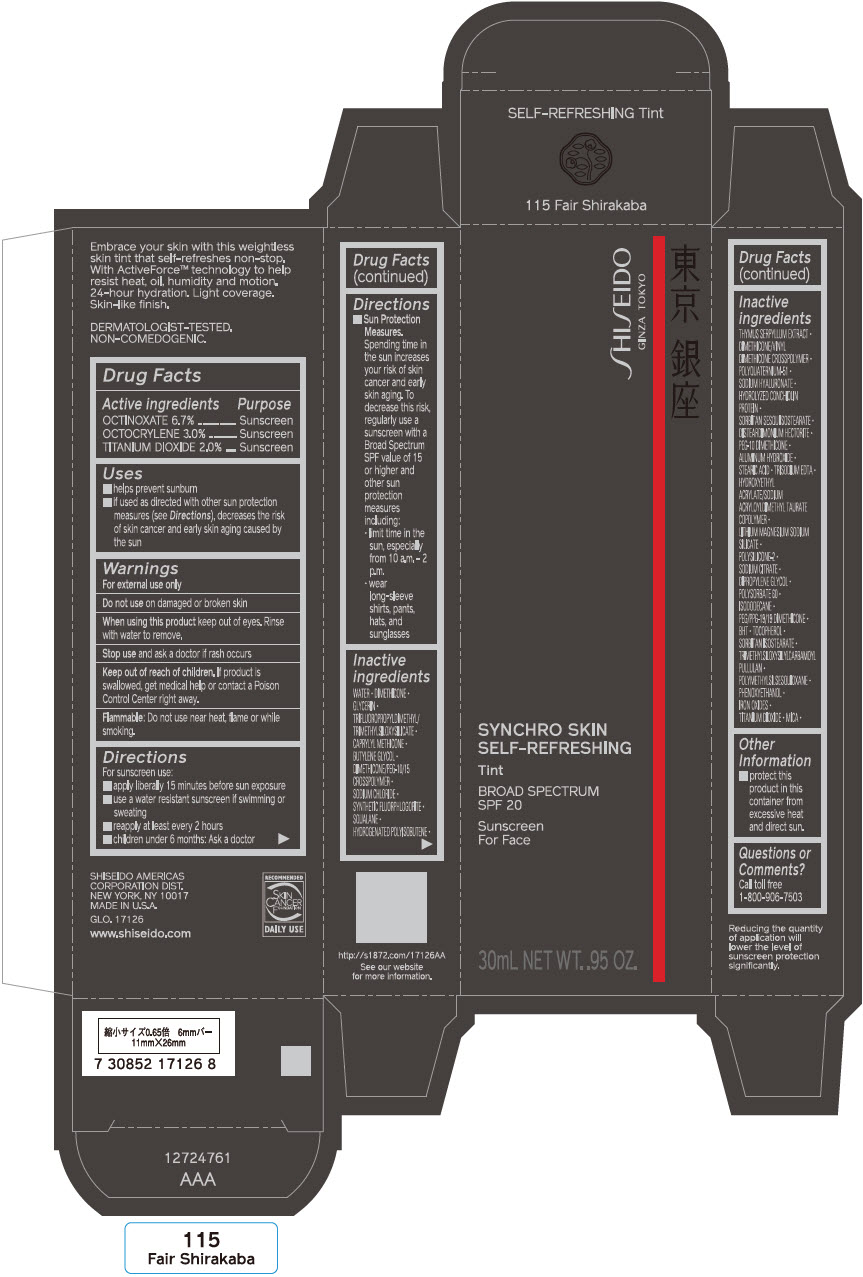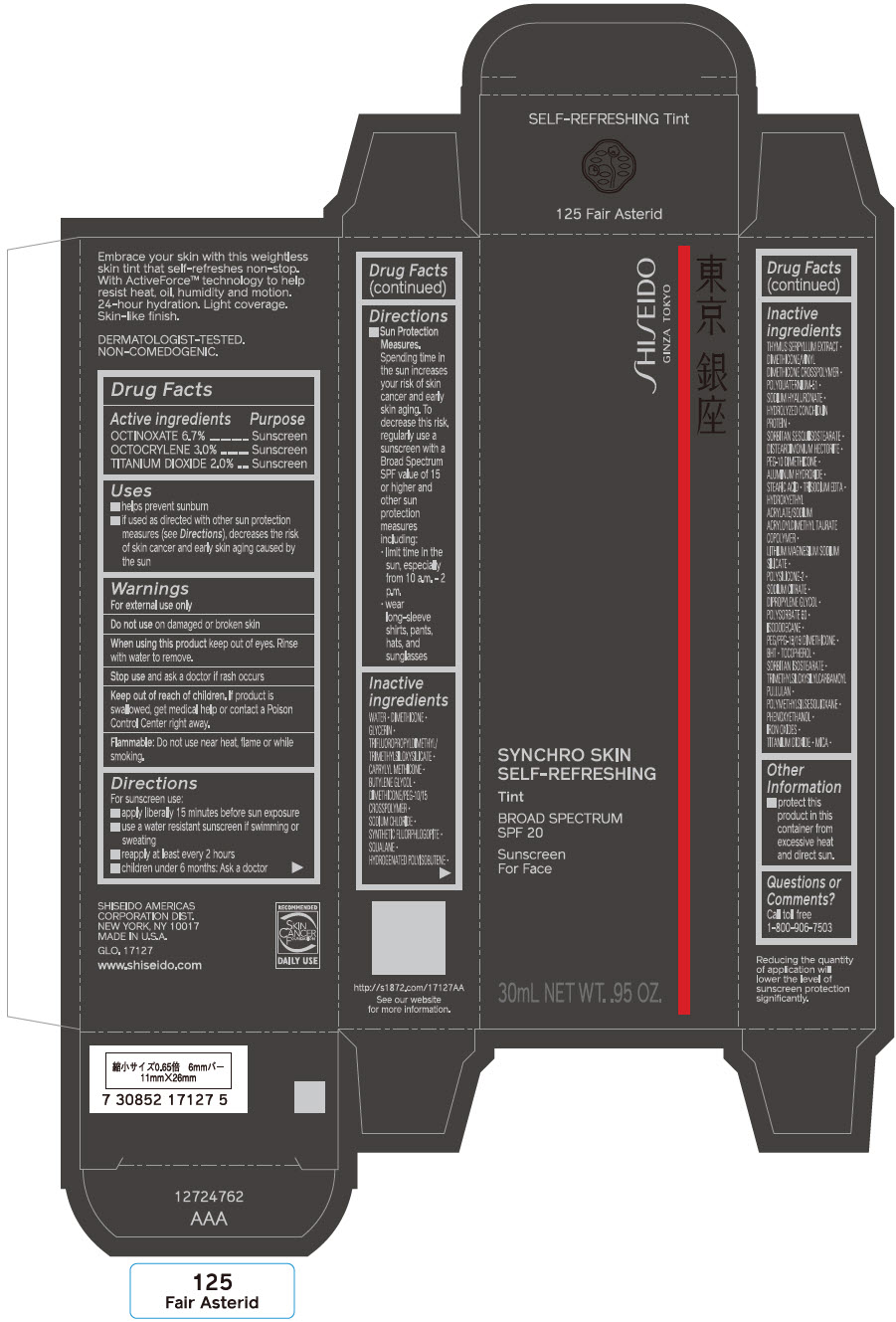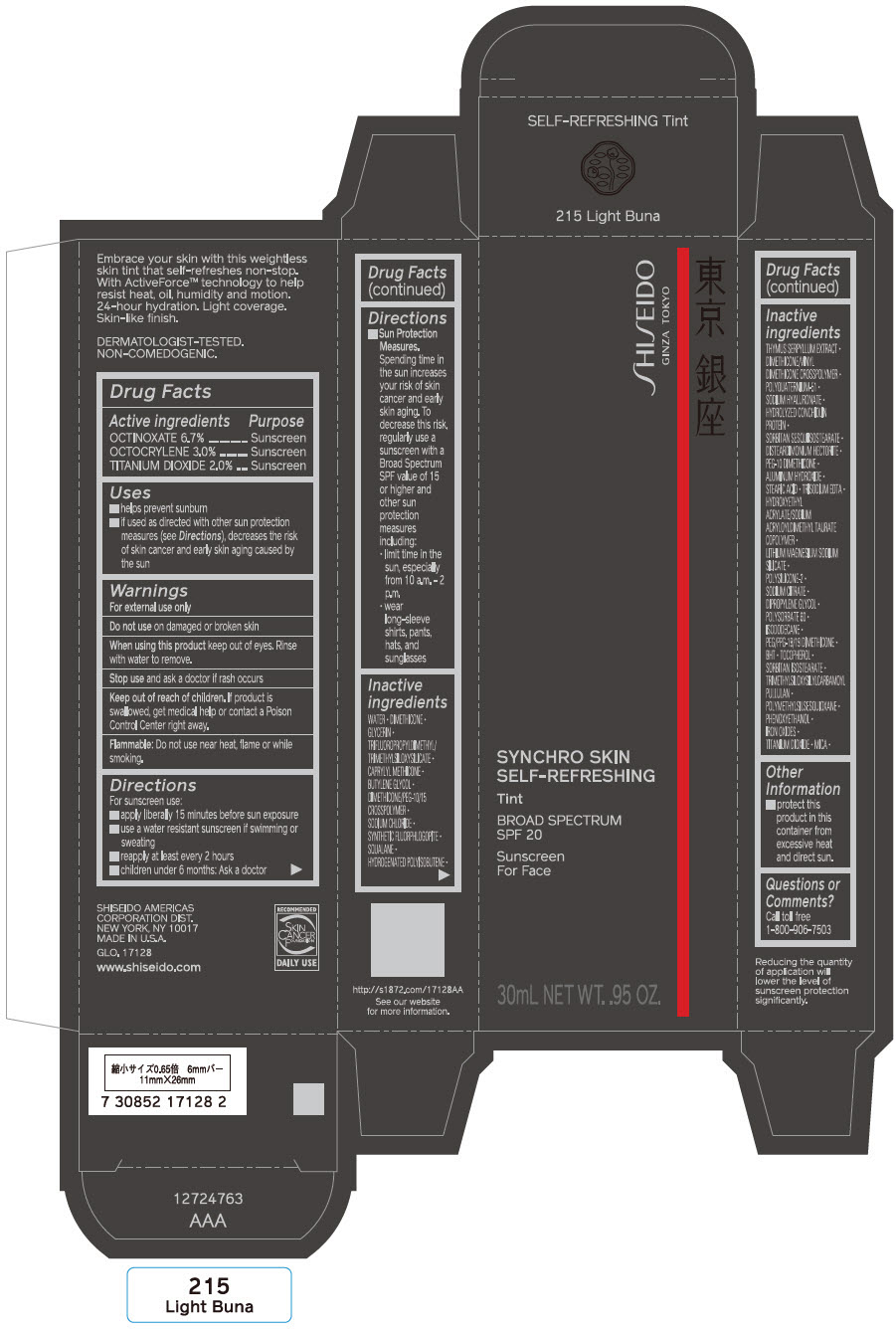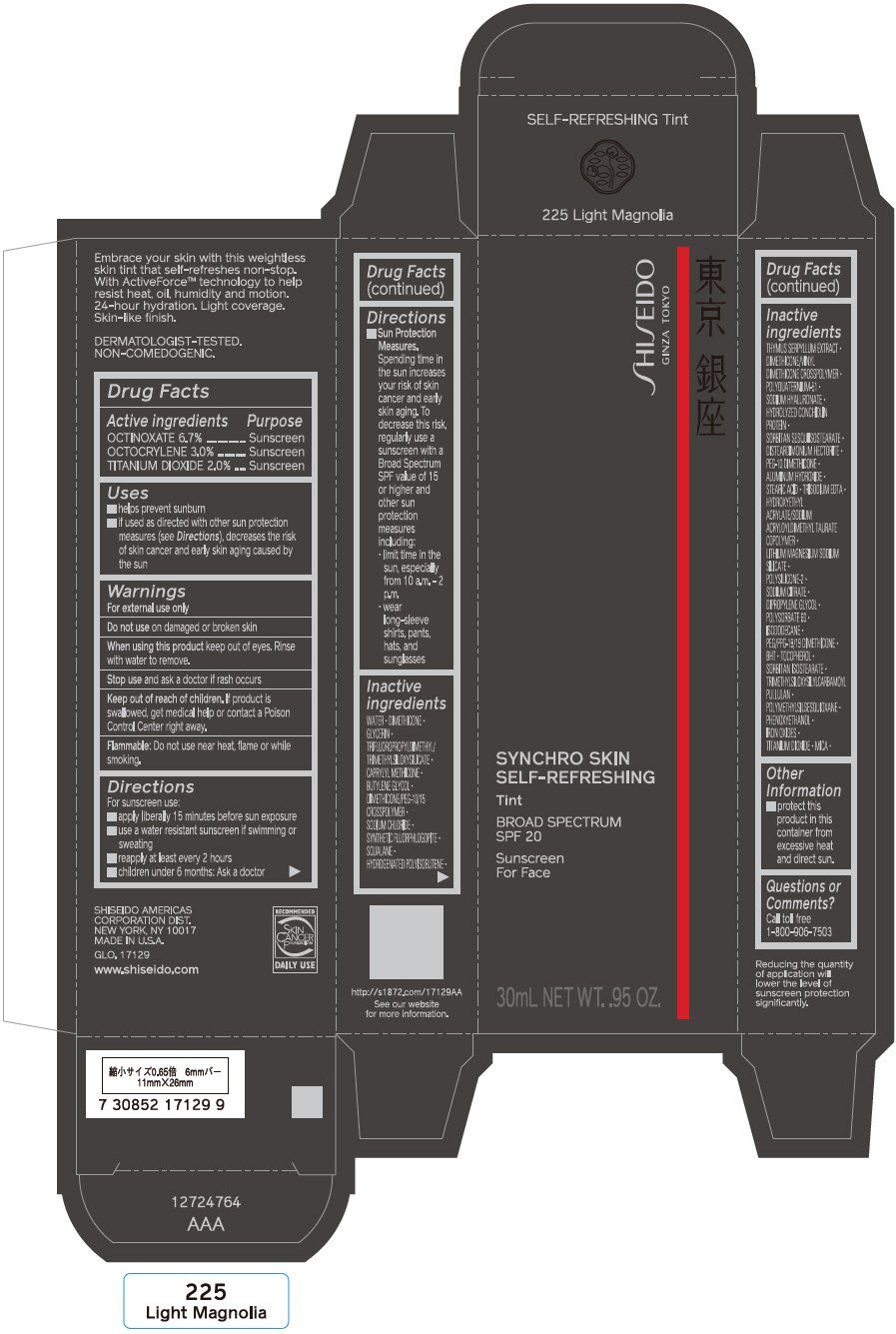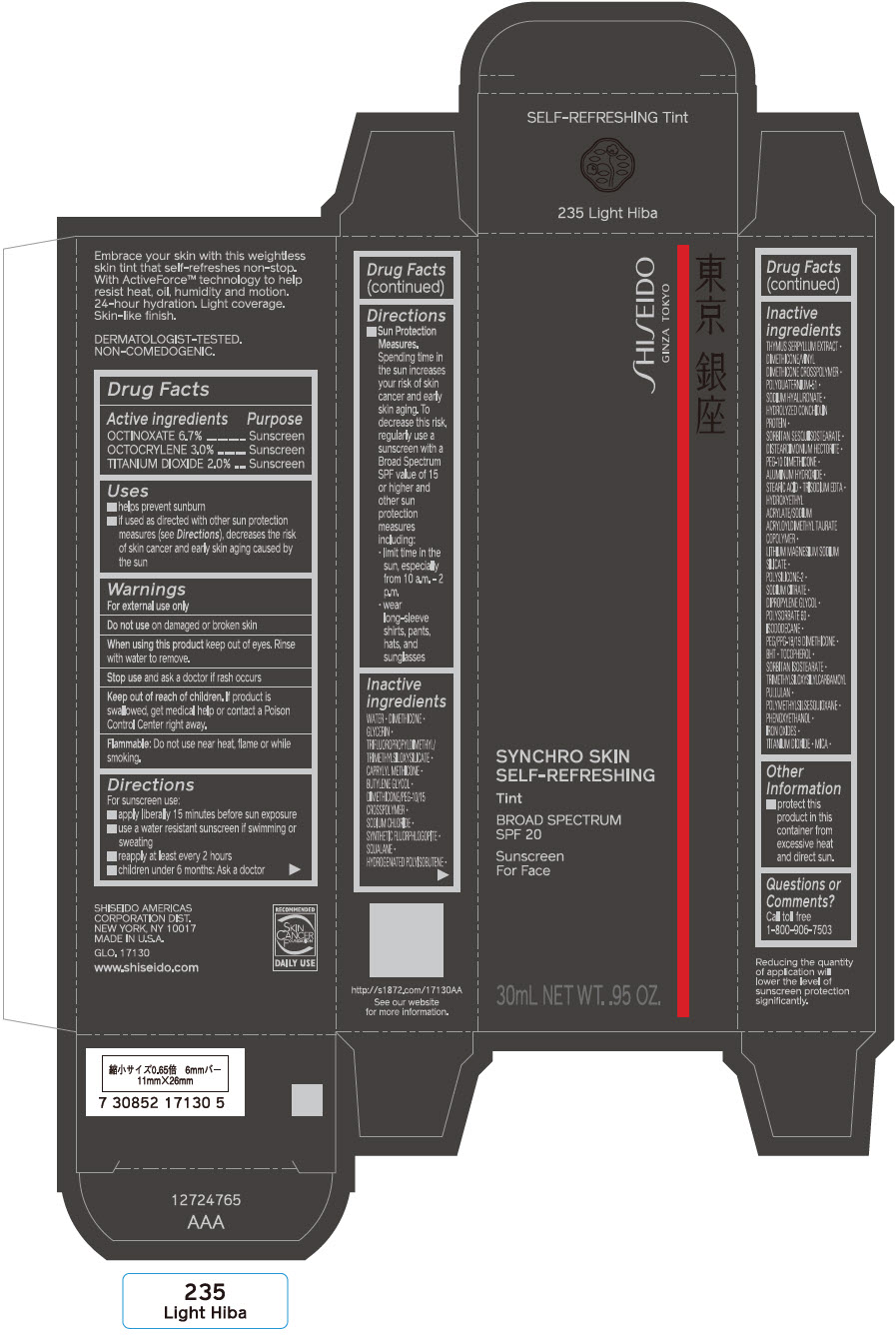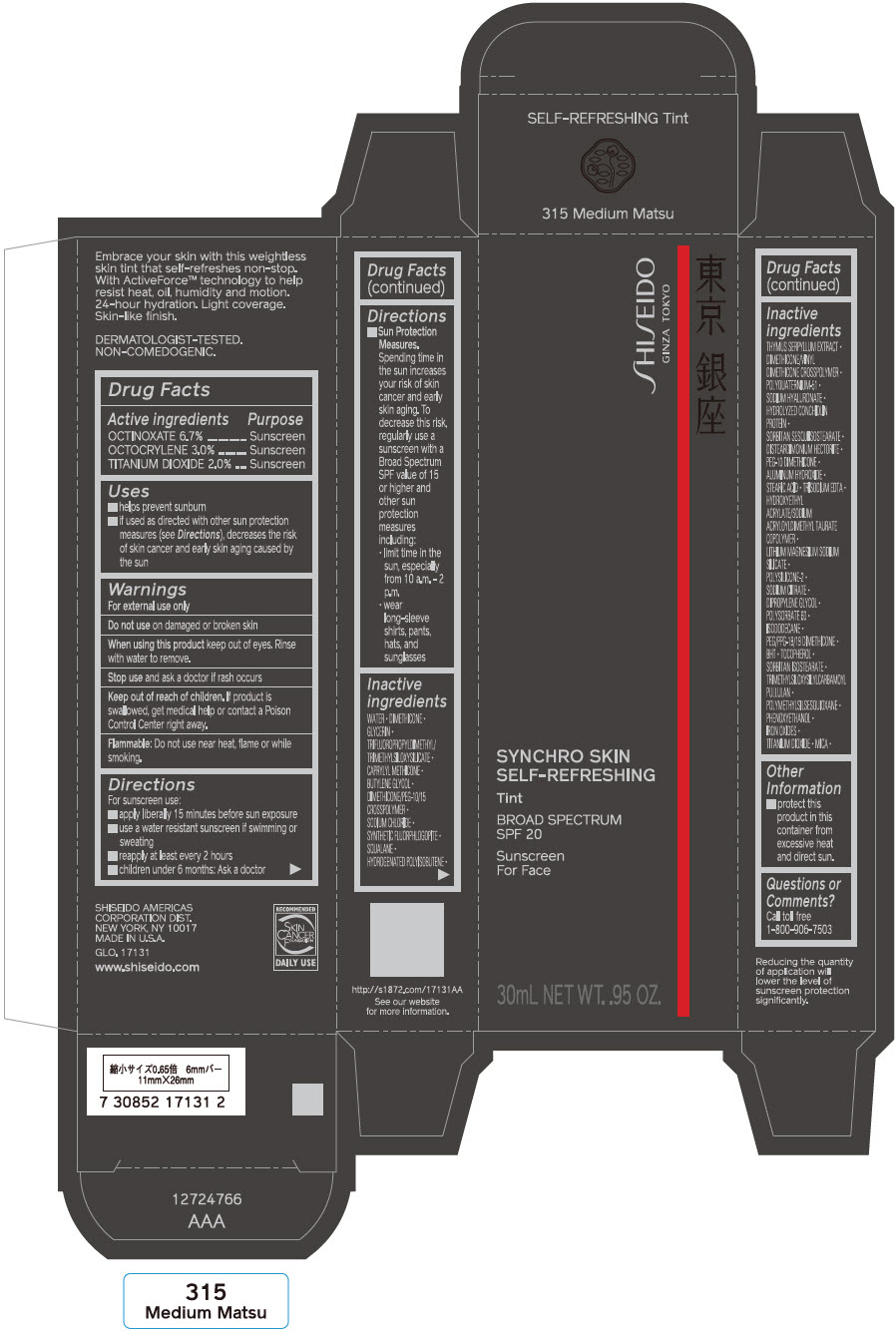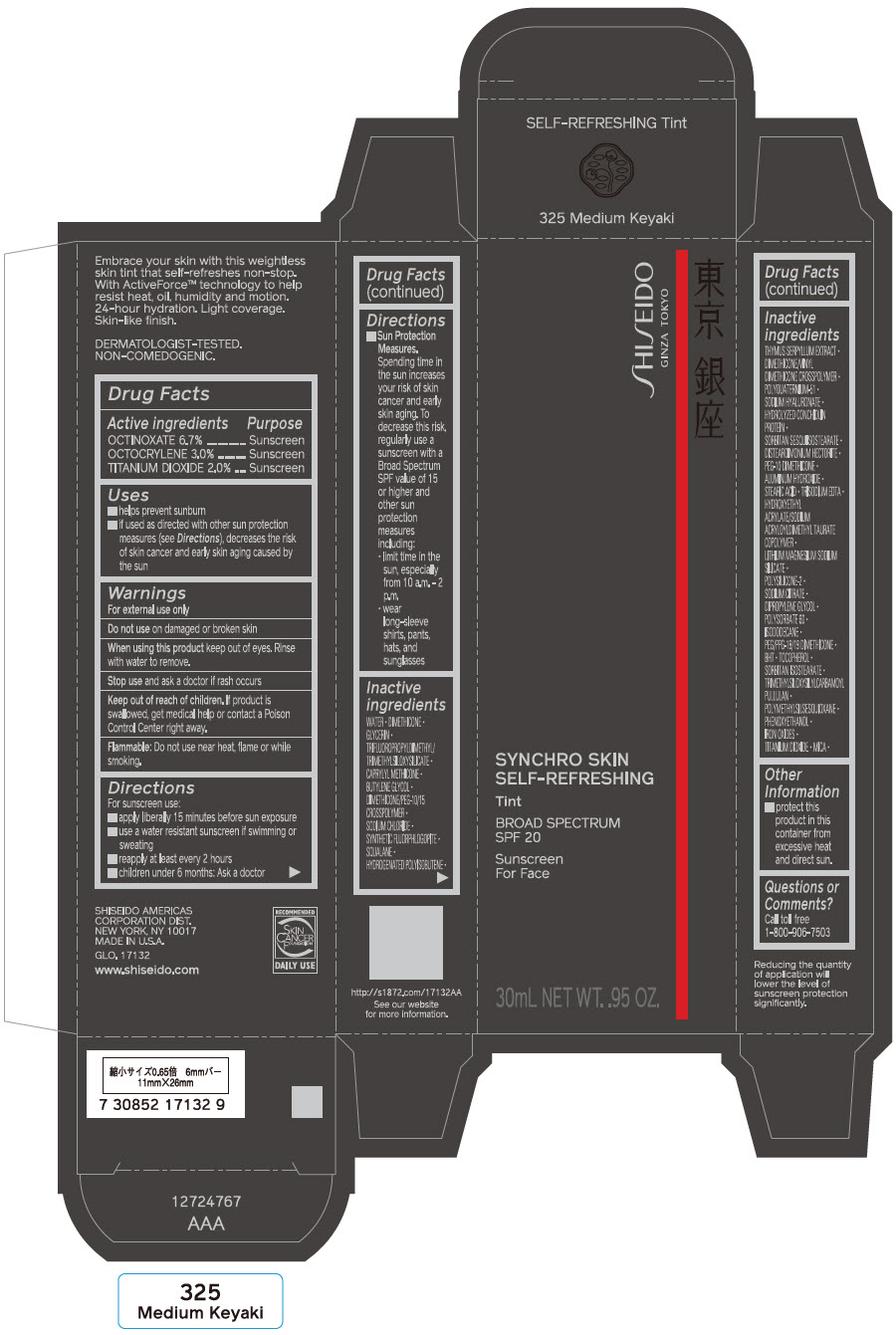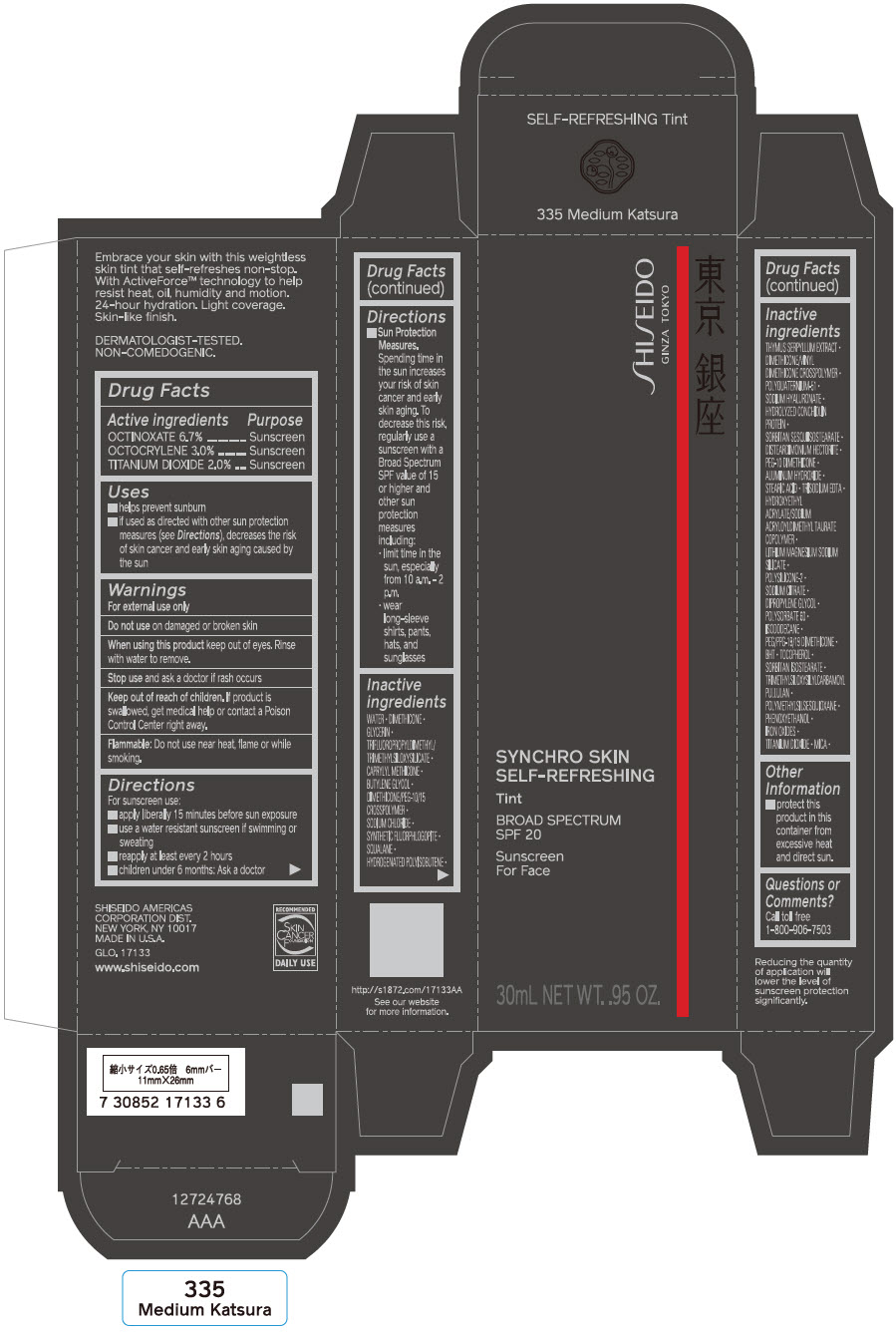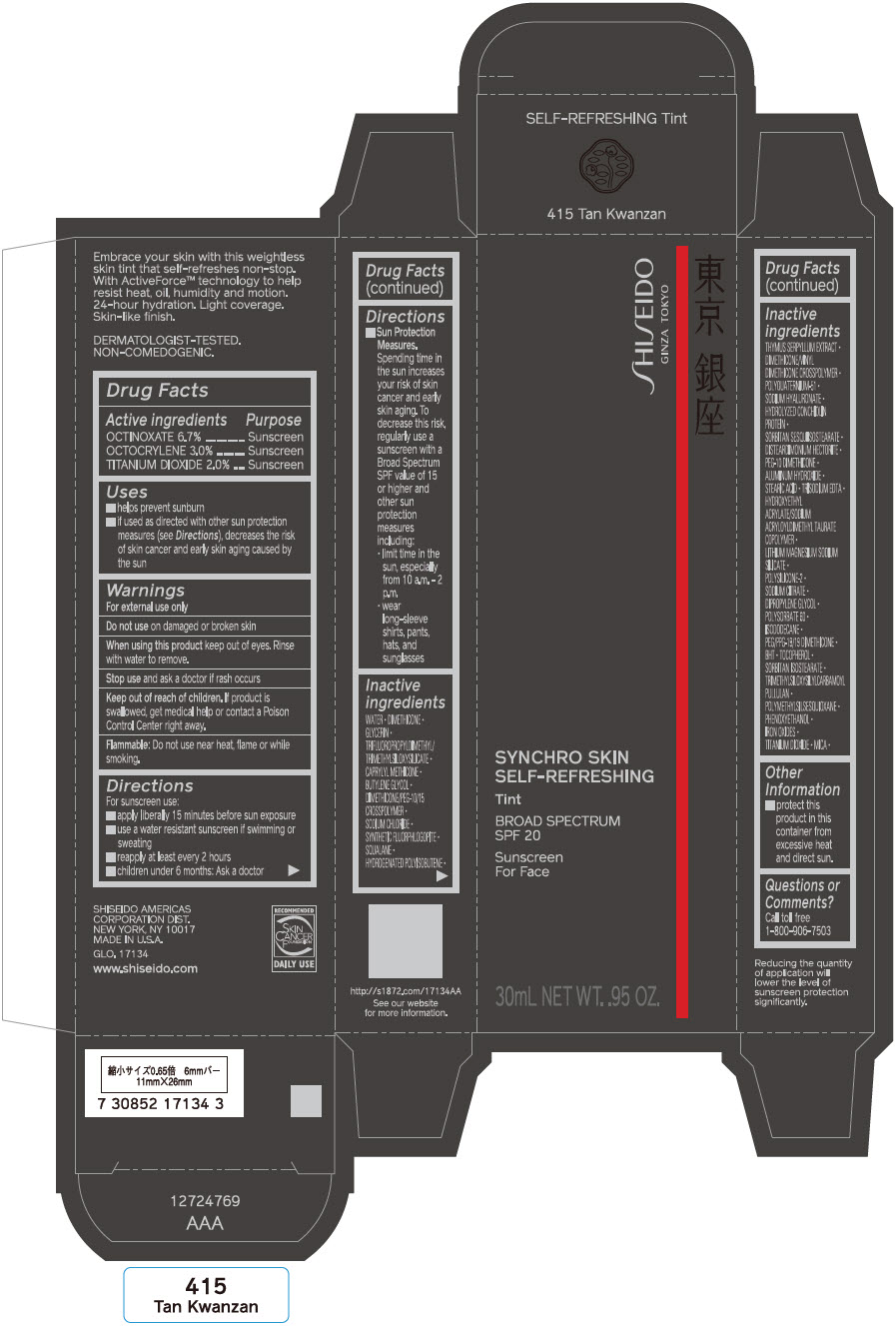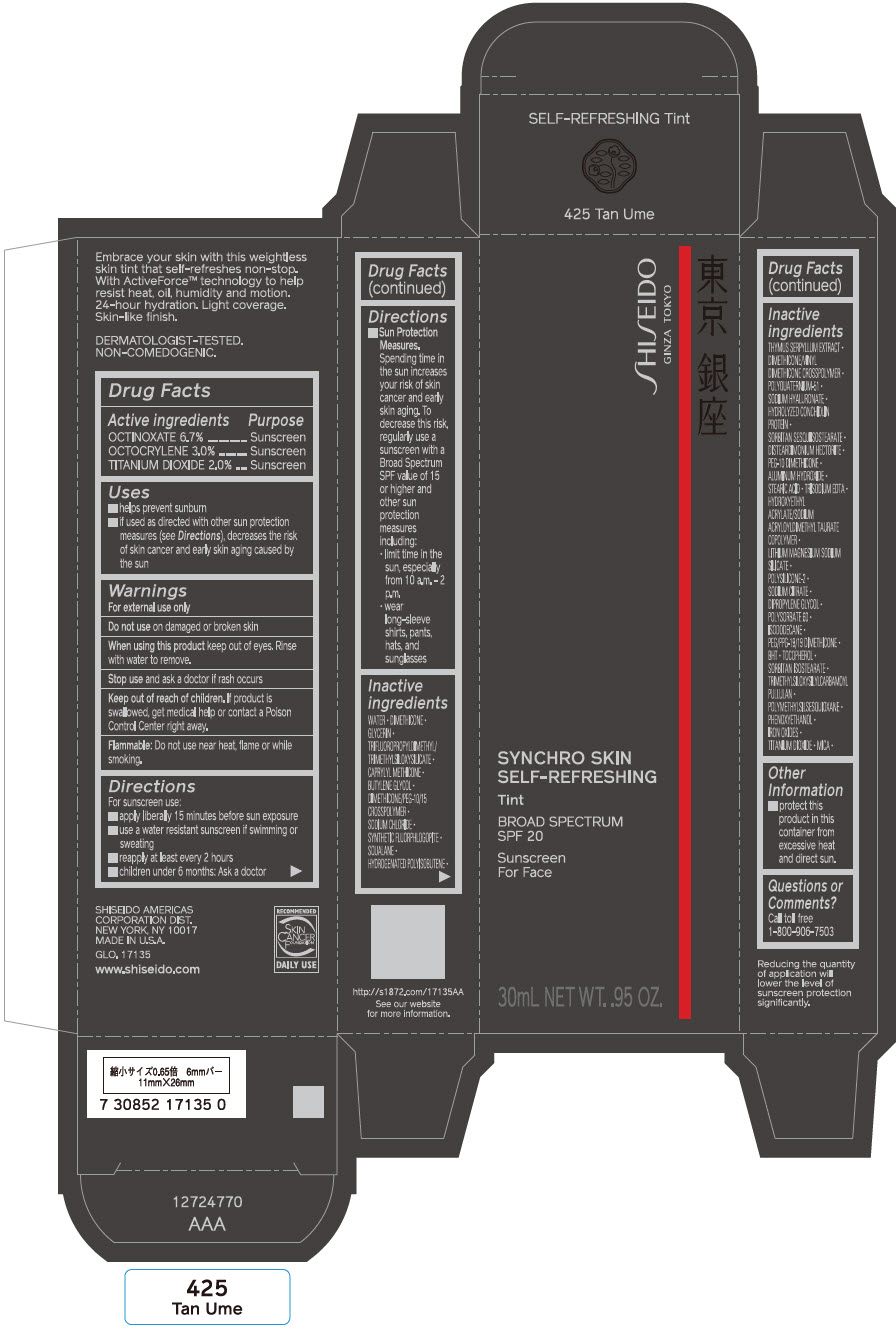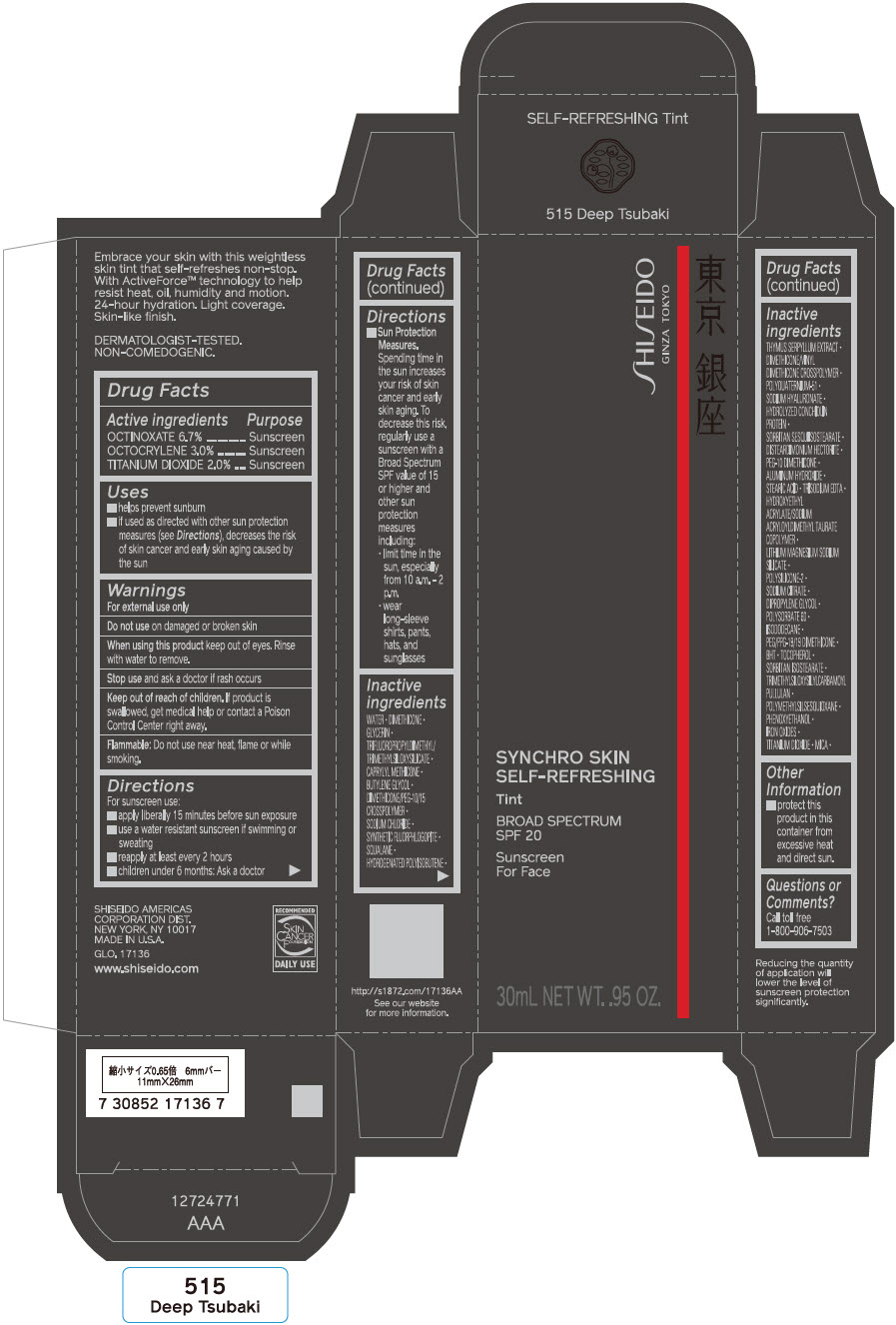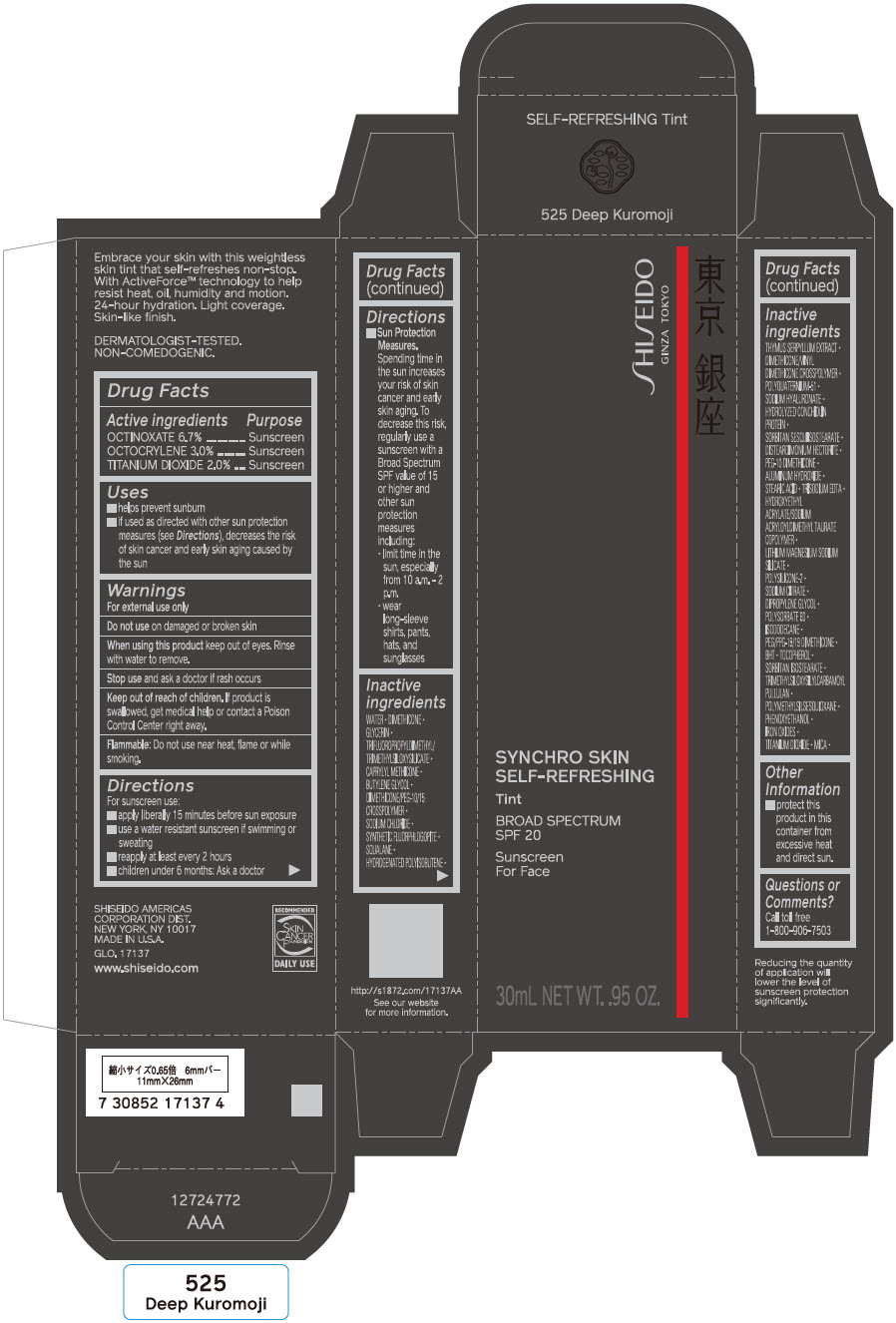 DRUG LABEL: SHISEIDO SYNCHRO SKIN SELF-REFRESHING TINT

NDC: 58411-673 | Form: EMULSION
Manufacturer: SHISEIDO AMERICAS CORPORATION
Category: otc | Type: HUMAN OTC DRUG LABEL
Date: 20260106

ACTIVE INGREDIENTS: OCTINOXATE 2010 mg/30 mL; OCTOCRYLENE 900 mg/30 mL; TITANIUM DIOXIDE 600 mg/30 mL
INACTIVE INGREDIENTS: WATER; DIMETHICONE; GLYCERIN; CAPRYLYL TRISILOXANE; BUTYLENE GLYCOL; FERRIC OXIDE YELLOW; FERRIC OXIDE RED; FERROSOFERRIC OXIDE; DIMETHICONE/PEG-10/15 CROSSPOLYMER; SODIUM CHLORIDE; MAGNESIUM POTASSIUM ALUMINOSILICATE FLUORIDE; SORBITAN SESQUIISOSTEARATE; PHENOXYETHANOL; DISTEARDIMONIUM HECTORITE; PEG-10 DIMETHICONE (600 CST); ALUMINUM HYDROXIDE; STEARIC ACID; EDETATE TRISODIUM; LAPONITE; SQUALANE; SODIUM CITRATE, UNSPECIFIED FORM; DIPROPYLENE GLYCOL; POLYSORBATE 60; ISODODECANE; PEG/PPG-19/19 DIMETHICONE; HYDROGENATED POLYISOBUTENE (1300 MW); BUTYLATED HYDROXYTOLUENE; MICA; TOCOPHEROL; SORBITAN ISOSTEARATE; THYMUS SERPYLLUM WHOLE; POLYMETHYLSILSESQUIOXANE (4.5 MICRONS); DIMETHICONE/VINYL DIMETHICONE CROSSPOLYMER (SOFT PARTICLE); POLYQUATERNIUM-51 (2-METHACRYLOYLOXYETHYL PHOSPHORYLCHOLINE/N-BUTYL METHACRYLATE; 3:7); HYALURONATE SODIUM

SHISEIDO SYNCHRO SKIN SELF-REFRESHING TINT

Drug Facts

ACTIVE INGREDIENT

Active ingredients | Purpose
Octinoxate 4.7% | Sunscreen
Octocrylene 3.0% | Sunscreen
Titanium Dioxide 2.0% | Sunscreen

Uses

- helps prevent sunburn
- if used as directed with other sun protection measures (see Directions), decreases the risk of skin cancer and early skin aging caused by the sun

Warnings

For external use only

Do not use ondamaged or broken skin

WHEN USING

When using this productkeep out of eyes. Rinse with water to remove.

Stop useand ask a doctor if rash occurs.

Keep out of reach of children.If product is swallowed, get medical help or contact a Poison Control Center right away.

Flammable

Do not use near heat, flame, or while smoking.

Directions

For sunscreen use:

- apply liberally 15 minutes before sun exposure
- use a water resistant sunscreen if swimming or sweating
- reapply at least every 2 hours
- children under 6 months: Ask a doctor
- Sun Protection Measures. Spending time in the sun increases your risk of skin cancer and early skin aging. To decrease this risk, regularly use a sunscreen with a broad spectrum SPF value of 15 or higher and other sun protection measures including:
  - limit time in the sun, especially from 10 a.m. – 2 p.m.
  - wear long-sleeve shirts, pants, hats, and sunglasses

Inactive Ingredients

WATER•DIMETHICONE•GLYCERIN•TRIFLUOROPROPYLDIMETHYL/TRIMETHYLSILOXYSILICATE•CAPRYLYL METHICONE•BUTYLENE GLYCOL•DIMETHICONE/PEG-10/15 CROSSPOLYMER•SODIUM CHLORIDE•SYNTHETIC FLUORHLOGOPITE•SQUALANE•HYDROGENATED POLYISOBUTENE•THYMUS SERPYLLUM EXTRACT•DIMETHICONE/VINYL DIMETHICONE CROSSPOLYMER•POLYQUATERNIUM-51•SODIUM HYALURONATE•HYDROLYZED CONCHIOLIN PROTEIN•SORBITAN SESQUIISOSTEARATE•DISTEARDIMONIUM HECTORITE•PEG-10 DIMETHICONE•ALUMINUM HYDROXIDE•STEARIC ACID•TRISODIUM EDTA•HYDROXYETHYL ACRYLATE/SODIUM ACRYLOYLDIMETHYL TAURATE COPOLYMER•LITHIUM MAGNESIUM SODIUM SILICATE•POLYSILICONE-2•SODIUM CITRATE•DIPROPYLENE GLYCOL•POLYSORBATE 60•ISODODECANE•PEG/PPG-19/19 DIMETHICONE•BHT•TOCOPHEROL•SORBITAN ISOSTEARATE•TRIMETHYLSILOXYSILYLCARBAMOYL PULLULAN•POLYMETHYLSILSESQUIOXANE•PHENOXYETHANOL•IRON OXIDES•TITANIUM DIOXIDE•MICA•

Other information

Protect this product in this container from excessive heat and direct sun.

Questions or comments?

Call toll free 1-800-906-7503

PRINCIPAL DISPLAY PANEL - 30 mL Bottle Carton - 115 Fair Shirakaba

SHISEIDO
GINZA TOKYO

SYNCHRO SKIN
SELF-REFRESHING

Tint

BROAD SPECTRUM
SPF 20

Sunscreen
For Face

30mL NET WT. .95 OZ.

PRINCIPAL DISPLAY PANEL - 30 mL Bottle Carton - 125 Fair Asterid

SHISEIDO
GINZA TOKYO

SYNCHRO SKIN
SELF-REFRESHING

Tint

BROAD SPECTRUM
SPF 20

Sunscreen
For Face

30mL NET WT. .95 OZ.

PRINCIPAL DISPLAY PANEL - 30 mL Bottle Carton - 215 Light Buna

SHISEIDO
GINZA TOKYO

SYNCHRO SKIN
SELF-REFRESHING

Tint

BROAD SPECTRUM
SPF 20

Sunscreen
For Face

30mL NET WT. .95 OZ.

PRINCIPAL DISPLAY PANEL - 30 mL Bottle Carton - 225 Light Magnolia

SHISEIDO
GINZA TOKYO

SYNCHRO SKIN
SELF-REFRESHING

Tint

BROAD SPECTRUM
SPF 20

Sunscreen
For Face

30mL NET WT. .95 OZ.

PRINCIPAL DISPLAY PANEL - 30 mL Bottle Carton - 235 Light Hiba

SHISEIDO
GINZA TOKYO

SYNCHRO SKIN
SELF-REFRESHING

Tint

BROAD SPECTRUM
SPF 20

Sunscreen
For Face

30mL NET WT. .95 OZ.

PRINCIPAL DISPLAY PANEL - 30 mL Bottle Carton - 315 Medium Matsu

SHISEIDO
GINZA TOKYO

SYNCHRO SKIN
SELF-REFRESHING

Tint

BROAD SPECTRUM
SPF 20

Sunscreen
For Face

30mL NET WT. .95 OZ.

PRINCIPAL DISPLAY PANEL - 30 mL Bottle Carton - 325 Medium Keyaki

SHISEIDO
GINZA TOKYO

SYNCHRO SKIN
SELF-REFRESHING

Tint

BROAD SPECTRUM
SPF 20

Sunscreen
For Face

30mL NET WT. .95 OZ.

PRINCIPAL DISPLAY PANEL - 30 mL Bottle Carton - 335 Medium Katsura

SHISEIDO
GINZA TOKYO

SYNCHRO SKIN
SELF-REFRESHING

Tint

BROAD SPECTRUM
SPF 20

Sunscreen
For Face

30mL NET WT. .95 OZ.

PRINCIPAL DISPLAY PANEL - 30 mL Bottle Carton - 415 Tan Kwanzan

SHISEIDO
GINZA TOKYO

SYNCHRO SKIN
SELF-REFRESHING

Tint

BROAD SPECTRUM
SPF 20

Sunscreen
For Face

30mL NET WT. .95 OZ.

PRINCIPAL DISPLAY PANEL - 30 mL Bottle Carton - 425 Tan Ume

SHISEIDO
GINZA TOKYO

SYNCHRO SKIN
SELF-REFRESHING

Tint

BROAD SPECTRUM
SPF 20

Sunscreen
For Face

30mL NET WT. .95 OZ.

PRINCIPAL DISPLAY PANEL - 30 mL Bottle Carton - 515 Deep Tsubaki

SHISEIDO
GINZA TOKYO

SYNCHRO SKIN
SELF-REFRESHING

Tint

BROAD SPECTRUM
SPF 20

Sunscreen
For Face

30mL NET WT. .95 OZ.

PRINCIPAL DISPLAY PANEL - 30 mL Bottle Carton - 525 Deep Kuromoji

SHISEIDO
GINZA TOKYO

SYNCHRO SKIN
SELF-REFRESHING

Tint

BROAD SPECTRUM
SPF 20

Sunscreen
For Face

30mL NET WT. .95 OZ.